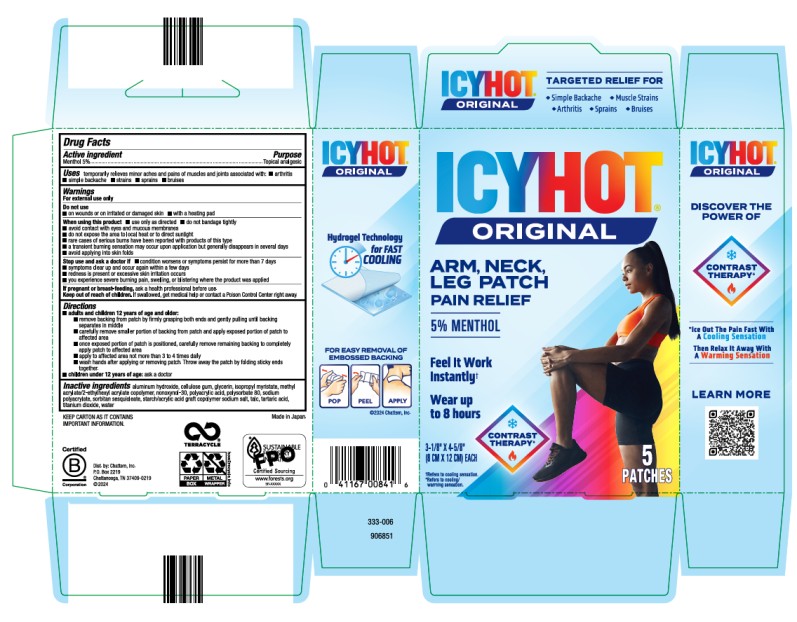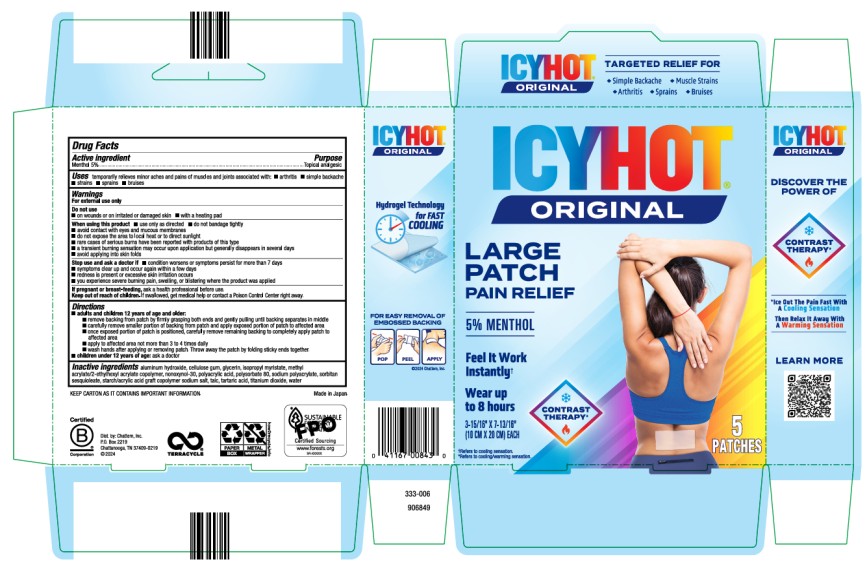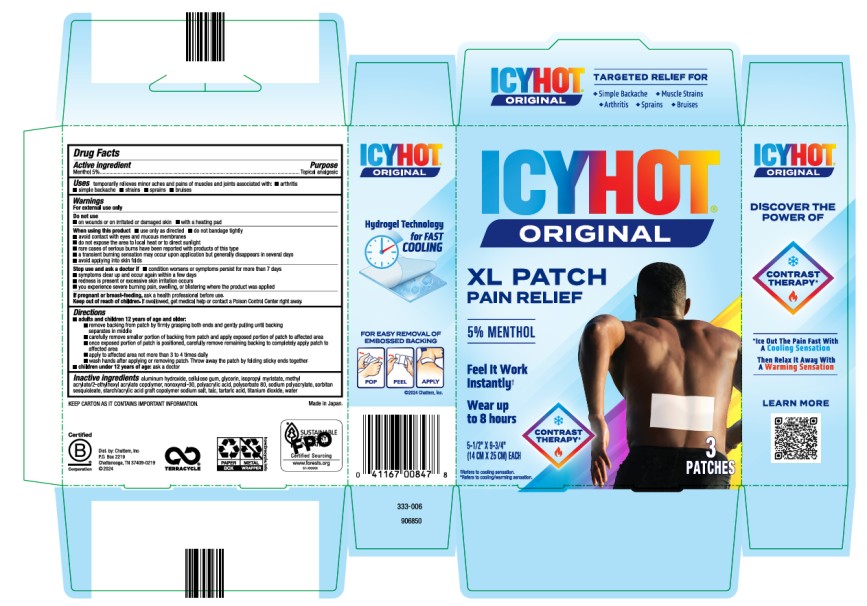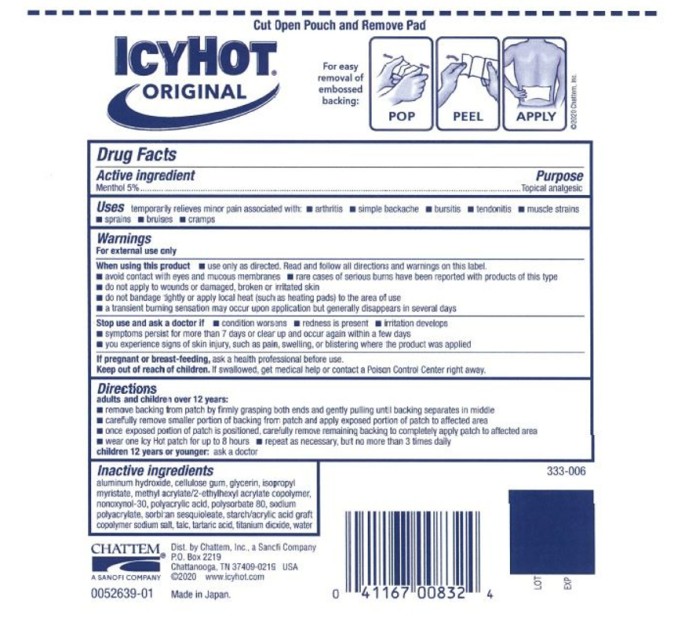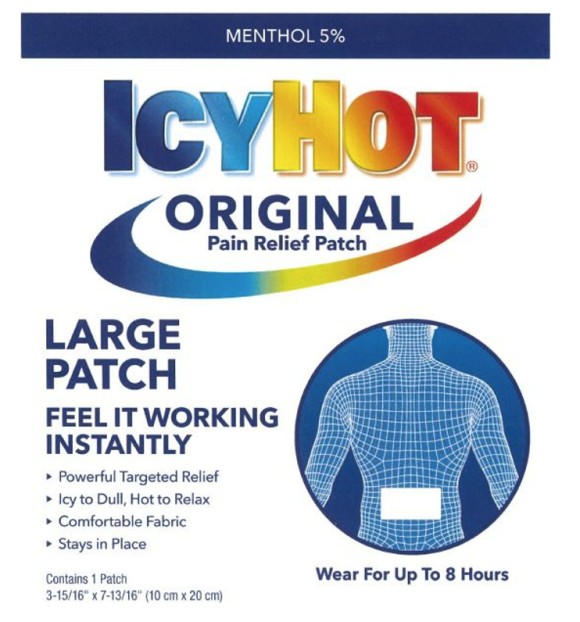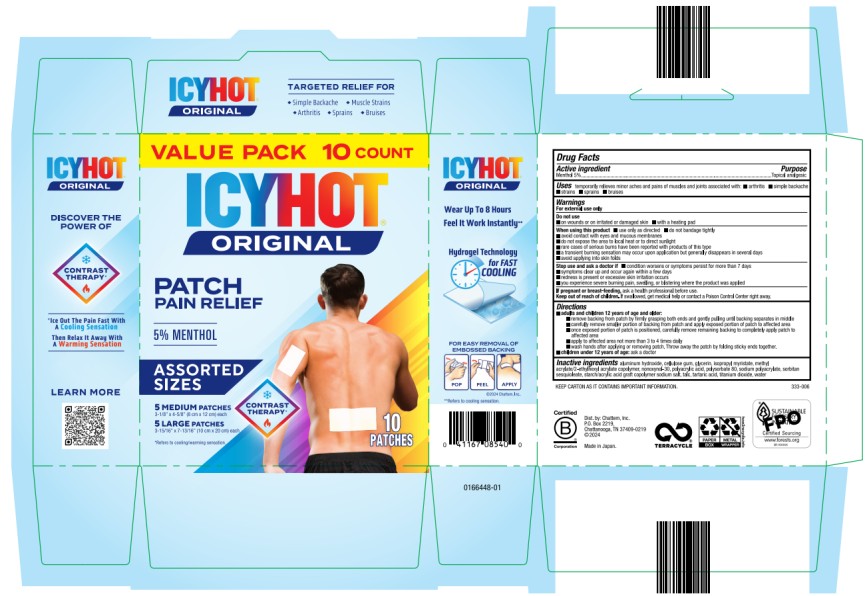 DRUG LABEL: Icy Hot Arm Neck Leg and Small Areas
NDC: 41167-0084 | Form: PATCH
Manufacturer: Chattem, Inc.
Category: otc | Type: HUMAN OTC DRUG LABEL
Date: 20250729

ACTIVE INGREDIENTS: MENTHOL 5 g/100 g
INACTIVE INGREDIENTS: ALUMINUM HYDROXIDE; CELLULOSE GUM; GLYCERIN; ISOPROPYL MYRISTATE; METHYL ACRYLATE; NONOXYNOL-30; POLYACRYLIC ACID (250000 MW); POLYSORBATE 80; SODIUM POLYACRYLATE (2500000 MW); SORBITAN SESQUIOLEATE; STARCH, CORN; ACRYLIC ACID; TALC; TARTARIC ACID; TITANIUM DIOXIDE; WATER

Icy Hot - Patch

Icy Hot® - Medicated Patch

ARM, NECK & LEG & SMALL AREAS

Active Ingredient

Menthol 5%

Purpose

Topical analgesic

Uses

temporarily relieves minor aches and pains of muscles and joints associated with:

- arthritis
- simple backache
- strains
- sprains
- bruises

Warnings

For external use only

Do not use

- on wounds or on irritated or damaged skin
- with a heating pad

When using this product

- use only as directed
- do not bandage tightly
- avoid contact with eyes and mucous membranes
- do not expose the area to local heat or to direct sunlight
- rare cases of serious burns have been reported with products of this type
- a transient burning sensation may occur upon application but generally disappears in several days
- avoid applying into skin folds

Stop use and ask a doctor if

- condition worsens or symptoms persist for more than 7 days
- symptoms clear up and occur again within a few days
- redness is present or excessive skin irritation occurs
- you experience severe burning pain, swelling, or blistering where the product was applied

If pregnant or breast-feeding

ask a health professional before use.

Keep out of reach of children.

If swallowed, get medical help or contact a Poison Control Center right away.

Directions

■ adults and children 12 years of age and older:

■ remove backing from patch by firmly grasping both ends and gently pulling until backing separates in middle

■ carefully remove smaller portion of backing from patch and apply exposed portion of patch to affected area

■ once exposed portion of patch is positioned, carefully remove remaining backing to completely apply patch to affected area

■ apply to the affected area not more than 3 to 4 times daily

■ wash hands after applying or removing patch. Throw away the patch by folding sticky ends together.

■ children under 12 years of age: ask a doctor

Inactive Ingredients

aluminum hydroxide, cellulose gum, glycerin, isopropyl myristate, methyl acrylate/2-ethylhexyl acrylate copolymer, nonoxynol-30, polyacrylic acid, polysorbate 80, sodium polyacrylate, sorbitan sesquioleate, starch/acrylic acid graft copolymer sodium salt, talc, tartaric acid, titanium dioxide, water

KEEP CARTON AS IT CONTAINS IMPORTANT INFORMATION FOR USAGE OF THE PRODUCT.

Distributed by Chattem, Inc.
P.O. Box 2219
Chattanooga, TN 37409-0219 USA
©2020 www.icyhot.com
Made in Japan.

Icy Hot® - Medicated Patch

BACK & LARGE AREAS

Active Ingredient

Menthol 5%

Purpose

Topical analgesic

Uses

temporarily relieves minor aches and pains of muscles and joints associated with:

- arthritis
- simple backache
- strains
- sprains
- bruises

Warnings

For external use only

Do not use

■ on wounds or on irritated or damaged skin

■ with a heating pad

When using this product

■ use only as directed

■ do not bandage tightly

■ avoid contact with eyes and mucous membranes

■ do not expose the area to local heat or to direct sunlight

■ rare cases of serious burns have been reported with products of this type

■ a transient burning sensation may occur upon application but generally disappears in several days

■ avoid applying into skin folds

Stop use and ask a doctor if

■ condition worsens or symptoms persist for more than 7 days

■ symptoms clear up and occur again within a few days

■ redness is present or excessive skin irritation occurs

■ you experience severe burning pain, swelling, or blistering where the product was applied

If pregnant or breast-feeding, ask a health professional before use.

Keep out of reach of children. If swallowed, get medical help or contact a Poison Control Center right away.

Directions

■ adults and children 12 years of age and older:

■ remove backing from patch by firmly grasping both ends and gently pulling until backing separates in middle

■ carefully remove smaller portion of backing from patch and apply exposed portion of patch to affected area

■ once exposed portion of patch is positioned, carefully remove remaining backing to completely apply patch to affected area

■ apply to affected area not more than 3 to 4 times daily

■ wash hands after applying or removing patch. Throw away the patch by folding sticky ends together.

■ children under 12 years of age: ask a doctor

Inactive Ingredients

aluminum hydroxide, cellulose gum, glycerin, isopropyl myristate, methyl acrylate/2-ethylhexyl acrylate copolymer, nonoxynol-30, polyacrylic acid, polysorbate 80, sodium polyacrylate, sorbitan sesquioleate, starch/acrylic acid graft copolymer sodium salt, talc, tartaric acid, titanium dioxide, water

KEEP CARTON AS IT CONTAINS IMPORTANT INFORMATION FOR USAGE OF THE PRODUCT.

Distributed by Chattem, Inc.
P.O. Box 2219
Chattanooga, TN 37409-0219 USA
©2020 www.icyhot.com
Made in Japan.

Icy Hot® - Medicated Patch

XL BACK & LARGE AREAS

Active Ingredient

Menthol 5%

Purpose

Topical analgesic

Uses

temporarily relieves minor aches and pains of muscles and joints associated with:

- arthritis
- simple backache
- strains
- sprains
- bruises

Warnings

For external use only

Do not use

■ on wounds or on irritated or damaged skin

■ with a heating pad

When using this product

- use only as directed
- do not bandage tightly
- avoid contact with eyes and mucous membranes
- do not expose the area to local heat or to direct sunlight
- rare cases of serious burns have been reported with products of this type
- a transient burning sensation may occur upon application but generally disappears in several days
- avoid applying into skin folds

Stop use and ask a doctor if

- condition worsens or symptoms persist for more than 7 days
- symptoms clear up and occur again within a few days
- redness is present or excessive skin irritation occurs
- you experience severe burning pain, swelling, or blistering where the product was applied

If pregnant or breast-feeding

ask a health professional before use.

Keep out of reach of children.

If swallowed, get medical help or contact a Poison Control Center right away.

Directions

■ adults and children 12 years of age and older:

■ remove backing from patch by firmly grasping both ends and gently pulling until backing separates in middle

■ carefully remove smaller portion of backing from patch and apply exposed portion of patch to affected area

■ once exposed portion of patch is positioned, carefully remove remaining backing to completely apply patch to affected area

■ apply to the affected area not more than 3 to 4 times daily

■ wash hands after applying or removing patch. Throw away the patch by folding sticky ends together.

■ children under 12 years of age: ask a doctor

Inactive Ingredients

aluminum hydroxide, cellulose gum, glycerin, isopropyl myristate, methyl acrylate/2-ethylhexyl acrylate copolymer, nonoxynol-30, polyacrylic acid, polysorbate 80, sodium polyacrylate, sorbitan sesquioleate, starch/acrylic acid graft copolymer sodium salt, talc, tartaric acid, titanium dioxide, water

KEEP CARTON AS IT CONTAINS IMPORTANT INFORMATION FOR USAGE OF THE PRODUCT.

Distributed by Chattem, Inc.
P.O. Box 2219
Chattanooga, TN 37409-0219 USA
©2020 www.icyhot.com
Made in Japan.

Icy Hot® - Medicated Patch

Value Pack

Active Ingredient

Menthol 5%

Purpose

Topical analgesic

Uses

temporarily relieves minor aches and pains of muscles and joints associated with:

- arthritis
- simple backache
- strains
- sprains
- bruises

Warnings

For external use only

Do not use

■ on wounds or on irritated or damaged skin

■ with a heating pad

When using this product

■ use only as directed

■ do not bandage tightly

■ avoid contact with eyes and mucous membranes

■ do not expose the area to local heat or to direct sunlight

■ rare cases of serious burns have been reported with products of this type

■ a transient burning sensation may occur upon application but generally disappears in several days

■ avoid applying into skin folds

Stop use and ask a doctor if

- condition worsens or symptoms persist for more than 7 days
- symptoms clear up and occur again within a few days
- redness is present or excessive skin irritation occurs
- you experience severe burning pain, swelling, or blistering where the product was applied

If pregnant or breast-feeding

ask a health professional before use.

Keep out of reach of children.

If swallowed, get medical help or contact a Poison Control Center right away.

Directions

- adults and children 12 years of age and older:
  ■ remove backing from patch by firmly grasping both ends and gently pulling until backing separates in middle
  ■ carefully remove smaller portion of backing from patch and apply exposed portion of patch to affected area
  ■ once exposed portion of patch is positioned, carefully remove remaining backing to completely apply patch to affected area
  ■ apply to affected area not more than 3 to 4 times daily
  ■ wash hands after applying or removing patch. Throw away the patch by folding sticky ends together.
- children under 12 years of age: ask a doctor

Inactive Ingredients

aluminum hydroxide, cellulose gum, glycerin, isopropyl myristate, methyl acrylate/2-ethylhexyl acrylate copolymer, nonoxynol-30, polyacrylic acid, polysorbate 80, sodium polyacrylate, sorbitan sesquioleate, starch/acrylic acid graft copolymer sodium salt, talc, tartaric acid, titanium dioxide, water

KEEP CARTON AS IT CONTAINS IMPORTANT INFORMATION

Distributed by Chattem, Inc.
P.O. Box 2219
Chattanooga, TN 37409-0219 USA
©2024
Made in Japan.

Principal Display Panel

ICY HOT®
ORIGINAL
ARM, NECK,
LEG PATCH
PAIN RELIEF
5% MENTHOL
Feel it Work Instantly
Wear for up to 8 Hours
3-1/8” x 4-5/8”
(8 CM x 12 CM) EACH
5 PATCHES

Principal Display Panel

ICY HOT®
ORIGINAL
LARGE PATCH
PAIN RELIEF
5% MENTHOL
3-15/16” x 7-13/16”
(10 cm x 20 cm) EACH
5 PATCHES

Principal Display Panel

ICY HOT®
ORIGINAL
XL PATCH
PAIN RELIEF
5% MENTHOL
Feel it Work Instantly
Wear for up to 8 Hours
5-1/2” x 9-3/4”
(14 CM x 25 CM) EACH
3 PATCHES

Principal Display Panel

ICY HOT®
ORIGINAL
Pain Relief Patch

Principal Display Panel

ICY HOT®
ORIGINAL
Pain Relief Patch
Menthol 5%

Principal Display Panel

ICY HOT
ORIGINAL
PATCH
PAIN RELIEF
5 % MENTHOL
ASSORTED SIZES
10 PATCHES